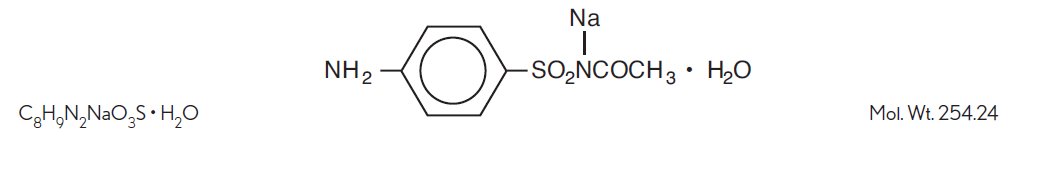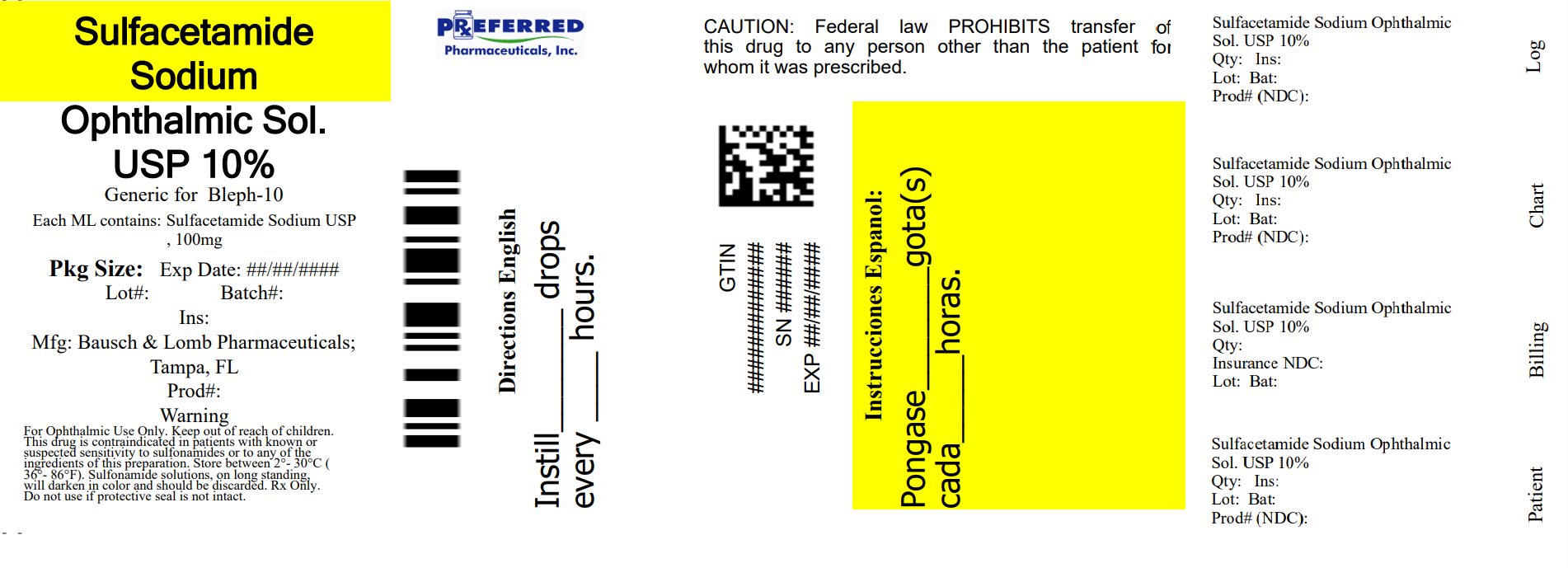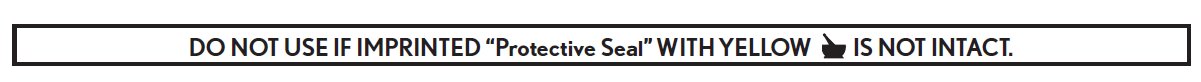 DRUG LABEL: Sulfacetamide Sodium
NDC: 68788-9871 | Form: SOLUTION/ DROPS
Manufacturer: Preferred Pharmaceuticals, Inc
Category: prescription | Type: HUMAN PRESCRIPTION DRUG LABEL
Date: 20250924

ACTIVE INGREDIENTS: SULFACETAMIDE SODIUM 100 mg/1 mL
INACTIVE INGREDIENTS: METHYLCELLULOSE (100 MPA.S); SODIUM THIOSULFATE; WATER; SODIUM PHOSPHATE, MONOBASIC, UNSPECIFIED FORM; METHYLPARABEN; PROPYLPARABEN

Sulfacetamide Sodium
Ophthalmic Solution, USP

10% (Sterile)

Rx only

FOR TOPICAL EYE USE ONLY

DESCRIPTION

Sulfacetamide sodium ophthalmic solution USP, 10% is a sterile, topical antibacterial agent for ophthalmic use. The active ingredient is represented by the following structural formula:

Chemical name: N-Sulfanilylacetamide monosodium salt monohydrate.

Each mL contains:

Active: sulfacetamide sodium, 100 mg/mL (10%);

Inactives: methylcellulose, purified water, sodium thiosulfate. Sodium phosphate monobasic may be added to adjust pH (6.8-8.0).

Preservatives: methylparaben 0.05% and propylparaben 0.01%. The osmolality range is 700-1300 mOsm/kg.

CLINICAL PHARMACOLOGY

Microbiology: The sulfonamides are bacteriostatic agents and the spectrum of activity is similar for all. Sulfonamides inhibit bacterial synthesis of dihydrofolic acid by preventing the condensation of the pteridine with aminobenzoic acid through competitive inhibition of the enzyme dihydropteroate synthetase. Resistant strains have altered dihydropteroate synthetase with reduced affinity for sulfonamides or produce increased quantities of aminobenzoic acid.

Topically applied sulfonamides are considered active against susceptible strains of the following common bacterial eye pathogens: Escherichia coli, Staphylococcus aureus, Streptococcus pneumoniae, Streptococcus (viridans group), Haemophilus influenzae, Klebsiella species, and Enterobacter species.

Topically applied sulfonamides do not provide adequate coverage against Neisseria species, Serratia marcescens and Pseudomonas aeruginosa. A significant percentage of staphylococcal isolates are completely resistant to sulfa drugs.

INDICATIONS AND USAGE

Sulfacetamide sodium ophthalmic solution USP, 10% is indicated for the treatment of conjunctivitis and other superficial ocular infections due to susceptible microorganisms, and as an adjunctive in systemic sulfonamide therapy of trachoma: Escherichia coli, Staphylococcus aureus, Streptococcus pneumoniae, Streptococcus (viridans group), Haemophilus influenzae, Klebsiella species, and Enterobacter species.

Topically applied sulfonamides do not provide adequate coverage against Neisseria species, Serratia marcescens and Pseudomonas aeruginosa. A significant percentage of staphylococcal isolates are completely resistant to sulfa drugs.

CONTRAINDICATIONS

Sulfacetamide sodium ophthalmic solution USP, 10% is contraindicated in individuals who have a hypersensitivity to sulfonamides or to any ingredient of the preparation.

WARNINGS

FOR TOPICAL EYE USE ONLY - NOT FOR INJECTION.

FATALITIES HAVE OCCURRED, ALTHOUGH RARELY, DUE TO SEVERE REACTIONS TO SULFONAMIDES INCLUDING STEVENS-JOHNSON SYNDROME, TOXIC EPIDERMAL NECROLYSIS, FULMINANT HEPATIC NECROSIS, AGRANULOCYTOSIS, APLASTIC ANEMIA AND OTHER BLOOD DYSCRASIAS. Sensitizations may recur when a sulfonamide is readministered, irrespective of the route of administration. Sensitivity reactions have been reported in individuals with no prior history of sulfonamide hypersensitivity. At the first sign of hypersensitivity, skin rash or other serious reaction, discontinue use of this preparation.

PRECAUTIONS

General

Prolonged use of topical antibacterial agents may give rise to overgrowth of nonsusceptible organisms including fungi. Bacterial resistance to sulfonamides may also develop.

The effectiveness of sulfonamides may be reduced by the para-aminobenzoic acid present in purulent exudates.

Sensitization may recur when a sulfonamide is readministered irrespective of the route of administration and cross-sensitivity between different sulfonamides may occur.

At the first sign of hypersensitivity, increase in purulent discharge, or aggravation of inflammation or pain, the patient should discontinue use of the medication and consult a physician (see WARNINGS).

Information for Patients

To avoid contamination, do not touch tip of container to the eye, eyelid or any surface.

Drug Interactions

Sulfacetamide preparations are incompatible with silver preparations.

Carcinogenesis, Mutagenesis, Impairment of Fertility

No studies have been conducted in animals or in humans to evaluate the possibility of these effects with ocularly administered sulfacetamide. Rats appear to be especially susceptible to the goitrogenic effects of sulfonamides, and long-term oral administration of sulfonamides has resulted in thyroid malignancies in these animals.

Pregnancy

Animal reproduction studies have not been conducted with sulfonamide ophthalmic preparations. Kernicterus may occur in the newborn as a result of treatment of a pregnant woman at term with orally administered sulfonamides. There are no adequate and well-controlled studies of sulfonamide ophthalmic preparations in pregnant women, and it is not known whether topically applied sulfonamides can cause fetal harm when administered to a pregnant woman. This product should be used in pregnancy only if the potential benefit justifies the potential risk to the fetus.

Nursing Mothers

Systemically administered sulfonamides are capable of producing kernicterus in infants of lactating women. Because of the potential for the development of kernicterus in neonates, a decision should be made whether to discontinue nursing or discontinue the drug taking into account the importance of the drug to the mother.

Pediatric Use

Safety and effectiveness in infants below the age of two months have not been established.

ADVERSE REACTIONS

Bacterial and fungal corneal ulcers have developed during treatment with sulfonamide ophthalmic preparations.

The most frequently reported reactions are local irritation, stinging and burning. Less commonly reported reactions include non-specific conjunctivitis, conjunctival hyperemia, secondary infections and allergic reactions.

Fatalities have occurred, although rarely, due to severe reactions to sulfonamides including Stevens-Johnson syndrome, toxic epidermal necrolysis, fulminant hepatic necrosis, agranulocytosis, aplastic anemia, and other blood dyscrasias (see WARNINGS).

To report SUSPECTED ADVERSE REACTIONS, contact Bausch & Lomb Incorporated at 1-800-553-5340 or FDA at 1-800-FDA-1088 or www.fda.gov/medwatch.

DOSAGE AND ADMINISTRATION

For conjunctivitis and other superficial ocular infections: Instill one or two drops into the conjunctival sac(s) of the affected eye(s) every two to three hours initially. Dosages may be tapered by increasing the time interval between doses as the condition responds. The usual duration of treatment is seven to ten days.

For trachoma: Instill two drops into the conjunctival sac(s) of the affected eye(s) every two hours. Topical administration must be accompanied by systemic administration.

HOW SUPPLIED

Sulfacetamide sodium ophthalmic solution USP, 10% is supplied in a plastic squeeze bottle with a controlled drop tip in the following size:

NDC 68788-9871-115 mL bottle

Storage: Store between 2°C to 25°C (36°F to 77°F).

Sulfonamide solutions, on long standing, will darken in color and should be discarded.

Keep out of reach of children.

Distributed by:
Bausch & Lomb Americas Inc.
Bridgewater, NJ 08807 USA

Manufactured by:
Bausch & Lomb Incorporated
Tampa, FL 33637 USA

© 2023 Bausch & Lomb Incorporated or its affiliates

Revised: August 2023

Relabeled By: Preferred Pharmaceuticals Inc.

PACKAGE/LABEL PRINCIPAL DISPLAY PANEL

NDC 68788-9871-1

Sulfacetamide
Sodium
Ophthalmic
Solution, USP
10%
(Sterile)

FOR TOPICAL
EYE USE ONLY

Eye image symbol

Rx only

15 mL

BAUSCH + LOMB

Relabeled By: Preferred Pharmaceuticals Inc.

9532102
AB0301